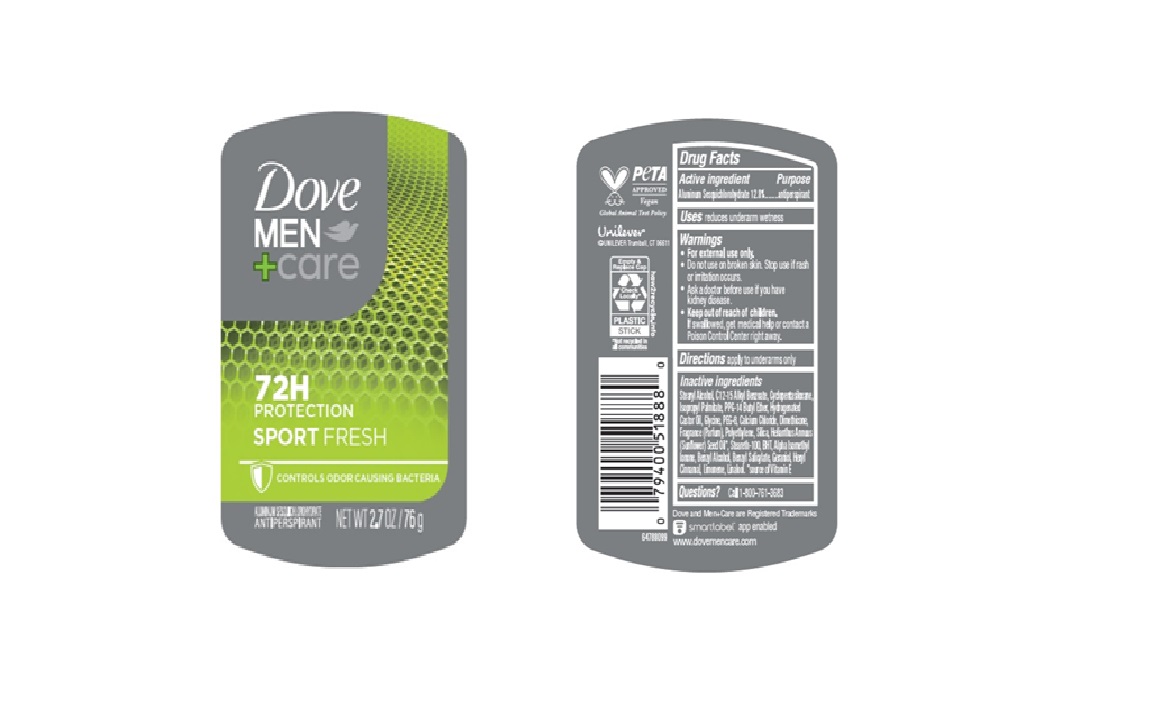 DRUG LABEL: Dove
NDC: 64942-2362 | Form: STICK
Manufacturer: Conopco d/b/a/ Unilever
Category: otc | Type: HUMAN OTC DRUG LABEL
Date: 20250331

ACTIVE INGREDIENTS: ALUMINUM SESQUICHLOROHYDRATE 12.8 g/100 g
INACTIVE INGREDIENTS: GERANIOL; HEXYL CINNAMAL; BENZYL SALICYLATE; BENZYL ALCOHOL; STEARETH-100; ISOPROPYL PALMITATE; BHT; ALPHA-ISOMETHYL IONONE; STEARYL ALCOHOL; C12-15 ALKYL BENZOATE; CYCLOPENTASILOXANE; CALCIUM CHLORIDE; DIMETHICONE; HELIANTHUS ANNUUS (SUNFLOWER) SEED OIL; PPG-14 BUTYL ETHER; HYDROGENATED CASTOR OIL; POLYETHYLENE; LINALOOL, (+/-)-; LIMONENE, (+)-; GLYCINE; PEG-8; SILICA

Dove Men + Care Sport Fresh 72H Antiperspirant

DESCRIPTION

Dove Men + Care Sport Fresh 72H Antiperspirant

ACTIVE INGREDIENT

Aluminum Sesquichlorohydrate (12.8%)

PURPOSE

Antiperspirant

INDICATIONS AND USAGE

reduces underarm wetness

WARNINGS

For external use only.

Do not use on broken skin.

Stop use if rash or irritation occurs.

Ask a doctor before use if you have kidney disease.

Keep out of reach of children. If swallowed, get medical help or contact a Poison Control Center right away.

DOSAGE AND ADMINISTRATION

Apply to underarms only

INACTIVE INGREDIENT

Stearyl Alcohol, C12-15 Alkyl Benzoate, Cyclopentasiloxane, Isopropyl Palmitate, PPG-14 Butyl Ether, Hydrogenated Castor Oil, Glycine, PEG-8, Calcium Chloride, Dimethicone, Fragrance (Parfum), Polyethylene, Silica, Helianthus Annuus (Sunflower) Seed Oil, Steareth-100, BHT, Alpha Isomethyl Ionone, Benzyl Alcohol, Benzyl Salicylate, Geraniol, Hexyl Cinnamal, Limonene, Linalool.

QUESTIONS

Call 1-800-761-3683